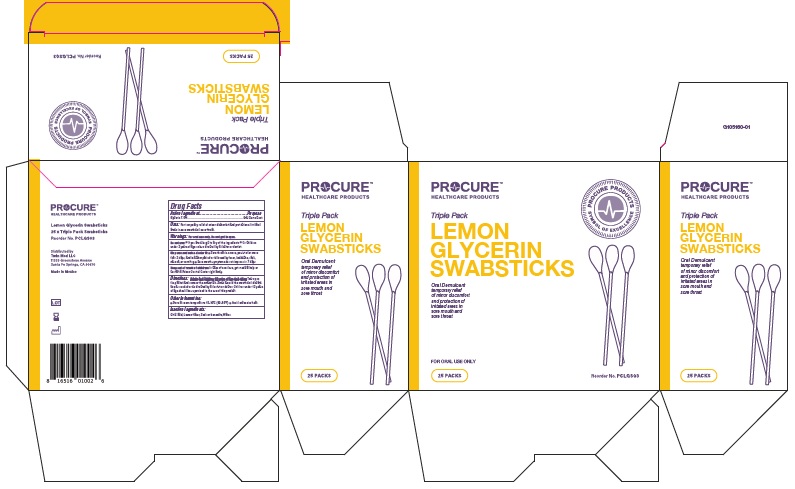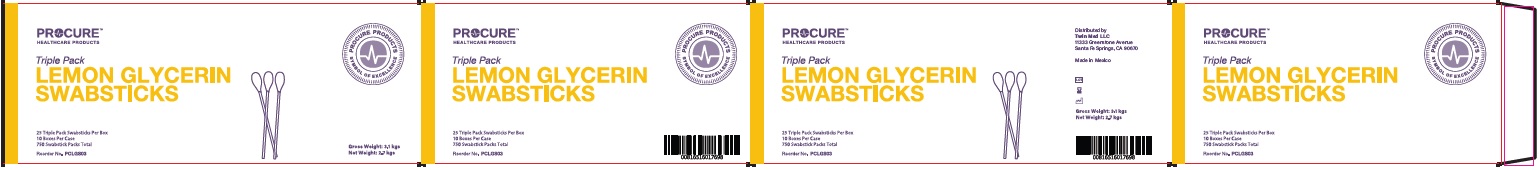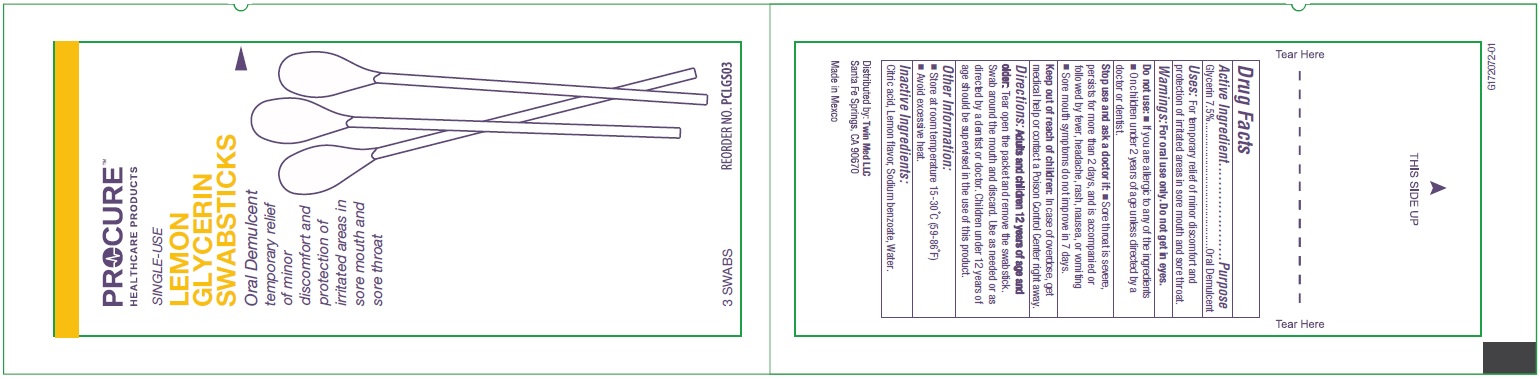 DRUG LABEL: Lemon
NDC: 55681-750 | Form: SWAB
Manufacturer: TwinMed LLC
Category: otc | Type: HUMAN OTC DRUG LABEL
Date: 20251218

ACTIVE INGREDIENTS: GLYCERIN 0.3 g/4 g
INACTIVE INGREDIENTS: SODIUM BENZOATE; CITRIC ACID MONOHYDRATE; WATER

Lemon Glycerin Swabsticks

Active Ingredient

Glycerin 7.5% v/v

Purpose

Oral Demulcent

Uses:

For temporary relief of minor discomfort and protection of irritated areas in sore mouth and sore throat.

Warnings:

For oral use only. Do not get in eyes.

Do not use:

- If you are allergic to any of the ingredients.
- On children under 2 years of age unless directed by a doctor or dentist.

Stop use and ask a doctor if:

- Sore throat is severe, persists for more than 2 days, and is accompanied or followed by fever, headache, rash, nausea, or vomiting
- Sore mouth symptoms do not improve in 7 days.

Keep out of reach of children:

In case of overdose, get medicl help or contact a Poison Control Center right away.

Directions:

Adults and children 12 years of age and older: Tear open the packet and remove the swabstick. Swab around the mouth and discard. Use as needed or as directed by a dentist or doctor. Children under 12 years of age should be supervised in the use of this product.

Other information

- Store at room temperature. 15C-30°C (59-86°F)
- Avoid excessive heat.

Inactive Ingredients

Citric acid, Lemon flavor, Sodium benzoate, Water

Principle Display Panel

PROCURE

HEALTHCARE PRODUCTS

Triple Pack

LEMON

GLYCERIN

SWABSTICKS

Oral Demulcent

temporary relief

of minor discomfort

and protection of

irritated areas in

sore mouth and

sore throat

FOR ORAL USE ONLY

25 PACKS